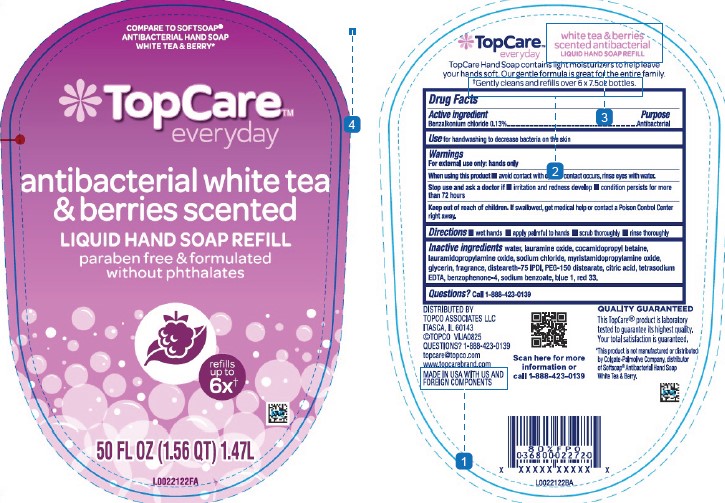 DRUG LABEL: ANTIBACTERIAL
NDC: 76162-897 | Form: LIQUID
Manufacturer: Topco Associates LLC
Category: otc | Type: HUMAN OTC DRUG LABEL
Date: 20260213

ACTIVE INGREDIENTS: BENZALKONIUM CHLORIDE 1.3 mg/1 mL
INACTIVE INGREDIENTS: PEG-150 DISTEARATE; DISTEARETH-75 ISOPHORONE DIISOCYANATE; LAURAMINE OXIDE; LAURAMIDOPROPYLAMINE OXIDE; GLYCERIN; SODIUM BENZOATE; WATER; COCAMIDOPROPYL BETAINE; D&C RED NO. 33; SODIUM CHLORIDE; MYRISTAMIDOPROPYLAMINE OXIDE; CITRIC ACID; EDETATE SODIUM; BENZOPHENONE-4; FD&C BLUE NO. 1

Top Care 897.003/897AC
Antibacterial Hand Soap Berries & White Tea

Claims

TopCare

everyday

white tea & berries scented antibacterial

LIQUID HAND SOAP REFILL

TopCare Hand Soap contains light moisturizers to help leave your hands soft. Our gentle formula is great for the entire family.

¥Gently cleans and refills over 6x 7.5 oz bottles.

Active ingredient

Benzalkonium chloride 0.13%

Purpose

Antibacterial

Use

for handwashing to decrease bacteria on the skin

Warnings

For external use only: hands only

When using this product

- avoid contact with eyes. If contact occurs, rinse eyes with water.

Stop use and ask a doctor if

- irritation and redness develop
- condition persists for more than 72 hours

Keep out of reach of children.

If swallowed, get medical help or contact a Poison Control Center right away.

Directions

- wet hands
- apply palmful to hands
- scrub thoroughly
- rinse thoroughly

Inactive ingredients

water, lauramine oxide, cocamidopropyl betaine, lauramidopropylamine oxide, sodium chloride, myristamidopropylamine oxide, glycerin, fragrance, disteareth-75 IPDI, PEG-150 distearate, citric acid, tetrasodium EDTA, benzophenone-4, sodium benzoate, blue 1, red 33

Questions?

Call 1-888-423-0139

Adverse Reaction

DISTRIBUTED BY TOPCO ASSOCIATES, LLC

ITASCA, IL 60143

©TOPCO VIJA0825

QUESTIONS? 1-888-423-0139

topcare@topco.com www.topcarebrands.com

MADE IN USA WITH US AND FOREIGN COMPONENTS

QUALITY GUARANTEED

This TopCare product is laboratory tested to guarantee its highest quality. Your total satisfaction is guaranteed.

Scan here for more information or call 1-888-423-0139

Disclaimer

*This product is not manufactured or distributed by Colgate-Palmolive Company, distributor of Softsoap® Antibacterial Hand Soap White Tea & Berry.

Principal Display Panel

COMPARE TO SOFTSOAP® ANTIBACTERIAL HAND SOAP WHITE TEA & BERRY*

TopCare™

everyday

antibacterial white tea & berries scented

LIQUID HAND SOAP REFILL

paraben free & formulated without phthalates

refills up to 6x¥

50 FL OZ (1.56 QT) 1.47 L